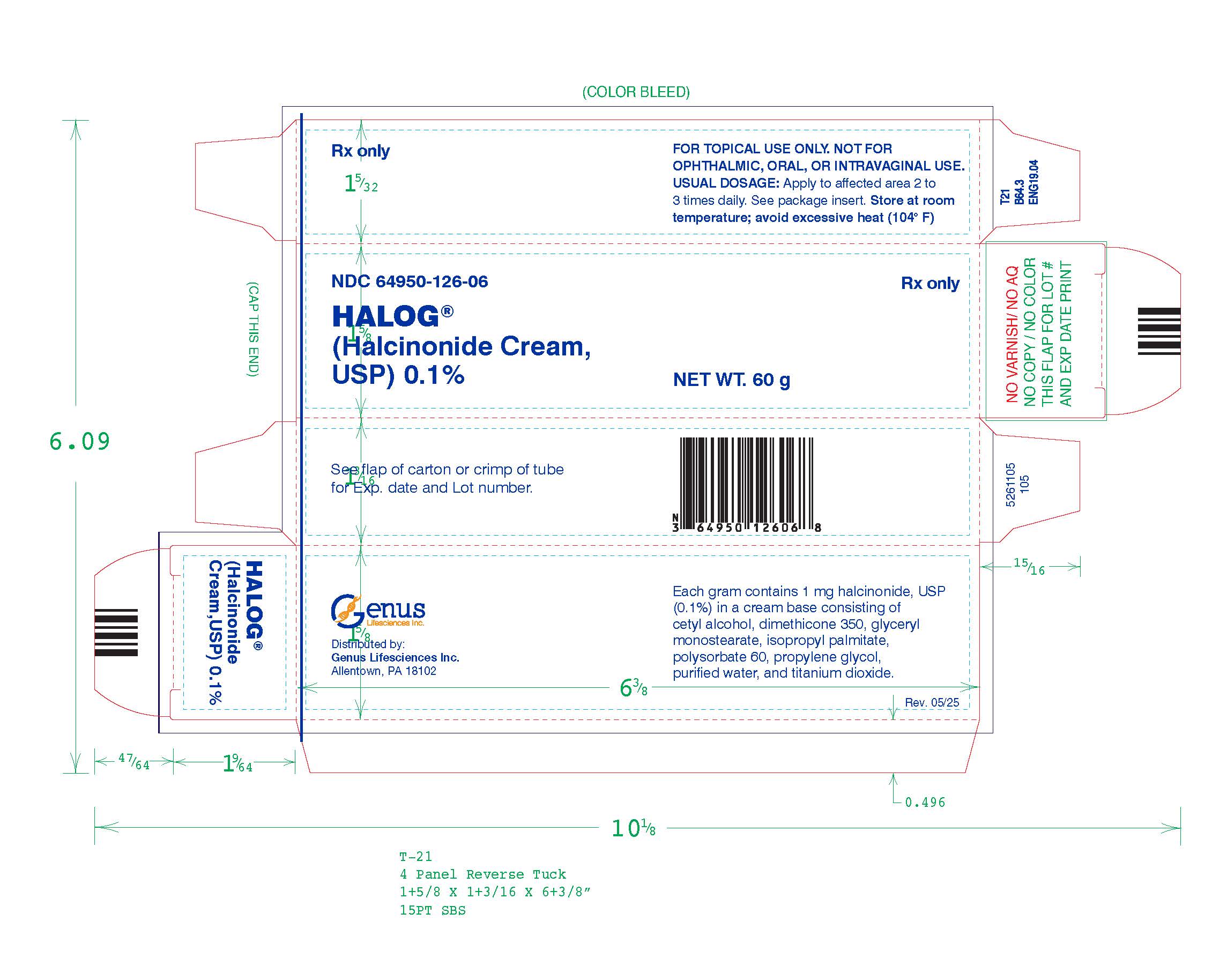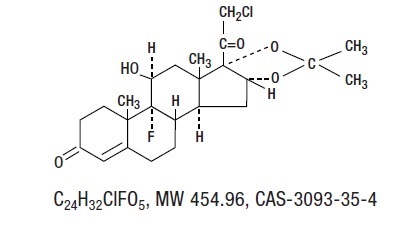 DRUG LABEL: Halog
NDC: 64950-126 | Form: CREAM
Manufacturer: Genus Lifesciences Inc.
Category: prescription | Type: HUMAN PRESCRIPTION DRUG LABEL
Date: 20260115

ACTIVE INGREDIENTS: HALCINONIDE 1 mg/1 g
INACTIVE INGREDIENTS: GLYCERYL MONOSTEARATE; CETYL ALCOHOL; ISOPROPYL PALMITATE; DIMETHICONE 350; POLYSORBATE 60; TITANIUM DIOXIDE; PROPYLENE GLYCOL; WATER

HALOG
(Halcinonide Cream, USP) 0.1%

FOR TOPICAL USE ONLY.

NOT FOR OPHTHALMIC, ORAL, OR INTRAVAGINAL USE.

DESCRIPTION

The topical corticosteroids constitute a class of primarily synthetic steroids used as anti-inflammatory and antipruritic agents. The steroids in this class include halcinonide. Halcinonide, USP is designated chemically as 21-Chloro-9-fluoro-11β, 16α, 17-trihydroxypregn-4-ene-3,20-dione cyclic 16,17-acetal with acetone. Graphic formula:

Each gram of 0.1% HALOG (Halcinonide Cream, USP) contains 1 mg halcinonide, USP in a specially formulated cream base consisting of cetyl alcohol, dimethicone 350, glyceryl monostearate, isopropyl palmitate, polysorbate 60, propylene glycol, purified water, and titanium dioxide.

CLINICAL PHARMACOLOGY

Topical corticosteroids share anti-inflammatory, antipruritic and vasoconstrictive actions.

The mechanism of anti-inflammatory activity of the topical corticosteroids is unclear. Various laboratory methods, including vasoconstrictor assays, are used to compare and predict potencies and/or clinical efficacies of the topical corticosteroids. There is some evidence to suggest that a recognizable correlation exists between vasoconstrictor potency and therapeutic efficacy in man.

Pharmacokinetics

The extent of percutaneous absorption of topical corticosteroids is determined by many factors including the vehicle, the integrity of the epidermal barrier, and the use of occlusive dressings.

Topical corticosteroids can be absorbed from normal intact skin. Inflammation and/or other disease processes in the skin increase percutaneous absorption. Occlusive dressings substantially increase the percutaneous absorption of topical corticosteroids. Thus, occlusive dressings may be a valuable therapeutic adjunct for treatment of resistant dermatoses (see DOSAGE AND ADMINISTRATION).

Once absorbed through the skin, topical corticosteroids are handled through pharmacokinetic pathways similar to systemically administered corticosteroids. Corticosteroids are bound to plasma proteins in varying degrees. Corticosteroids are metabolized primarily in the liver and are then excreted by the kidneys. Some of the topical corticosteroids and their metabolites are also excreted into the bile.

INDICATIONS AND USAGE

HALOG (Halcinonide Cream, USP) 0.1% is indicated for the relief of the inflammatory and pruritic manifestations of corticosteroid-responsive dermatoses.

CONTRAINDICATIONS

Topical corticosteroids are contraindicated in those patients with a history of hypersensitivity to any of the components of the preparations.

PRECAUTIONS

General

Systemic absorption of topical corticosteroids has produced reversible hypothalamic-pituitary-adrenal (HPA) axis suppression, manifestations of Cushing’s syndrome, hyperglycemia, and glucosuria in some patients.

Conditions which augment systemic absorption include the application of the more potent steroids, use over large surface areas, prolonged use, and the addition of occlusive dressings.

Therefore, patients receiving a large dose of any potent topical steroid applied to a large surface area or under an occlusive dressing should be evaluated periodically for evidence of HPA axis suppression by using the urinary free cortisol and ACTH stimulation tests, and for impairment of thermal homeostasis. If HPA axis suppression or elevation of the body temperature occurs, an attempt should be made to withdraw the drug, to reduce the frequency of application, substitute a less potent steroid, or use a sequential approach when utilizing the occlusive technique.

Recovery of HPA axis function and thermal homeostasis are generally prompt and complete upon discontinuation of the drug. Infrequently, signs and symptoms of steroid withdrawal may occur, requiring supplemental systemic corticosteroids. Occasionally, a patient may develop a sensitivity reaction to a particular occlusive dressing material or adhesive and a substitute material may be necessary.

Children may absorb proportionally larger amounts of topical corticosteroids and thus be more susceptible to systemic toxicity (see PRECAUTIONS: Pediatric Use).

If irritation develops, topical corticosteroids should be discontinued and appropriate therapy instituted.

In the presence of dermatological infections, the use of an appropriate antifungal or antibacterial agent should be instituted. If a favorable response does not occur promptly, the corticosteroid should be discontinued until the infection has been adequately controlled.

This preparation is not for ophthalmic, oral, or intravaginal use.

Information for the Patient

Patients using topical corticosteroids should receive the following information and instructions:

1. This medication is to be used as directed by the physician. It is for dermatologic use only. Avoid contact with the eyes.

2. Patients should be advised not to use this medication for any disorder other than for which it was prescribed.

3. The treated skin area should not be bandaged or otherwise covered or wrapped as to be occlusive unless directed by the physician.

4. Patients should report any signs of local adverse reactions especially under occlusive dressing.

5. Parents of pediatric patients should be advised not to use tight-fitting diapers or plastic pants on a child being treated in the diaper area, as these garments may constitute occlusive dressings.

Laboratory Tests

A urinary free cortisol test and ACTH stimulation test may be helpful in evaluating HPA axis suppression.

Carcinogenesis, and Mutagenesis, and Impairment of Fertility

Long-term animal studies have not been performed to evaluate the carcinogenic potential or the effect on fertility of topical corticosteroids.

Studies to determine mutagenicity with prednisolone and hydrocortisone showed negative results.

Pregnancy

Teratogenic Effects

Corticosteroids are generally teratogenic in laboratory animals when administered systemically at relatively low dosage levels. The more potent corticosteroids have been shown to be teratogenic after dermal application in laboratory animals. There are no adequate and well-controlled studies in pregnant women on teratogenic effects from topically applied corticosteroids. Therefore, topical corticosteroids should be used during pregnancy only if the potential benefit justifies the potential risk to the fetus. Drugs of this class should not be used extensively on pregnant patients, in large amounts, or for prolonged periods of time.

Nursing Mothers

It is not known whether topical administration of corticosteroids could result in sufficient systemic absorption to produce detectable quantities in breast milk. Systemically administered corticosteroids are secreted into breast milk in quantities not likely to have a deleterious effect on the infant. Nevertheless, caution should be exercised when topical corticosteroids are administered to a nursing woman.

Pediatric Use

Pediatric patients may demonstrate greater susceptibility to topical corticosteroid-induced HPA axis suppression and Cushing’s syndrome than mature patients because of a larger skin surface area to body weight ratio.

HPA axis suppression, Cushing’s syndrome, and intracranial hypertension have been reported in children receiving topical corticosteroids. Manifestations of adrenal suppression in children include linear growth retardation, delayed weight gain, low plasma cortisol levels, and absence of response to ACTH stimulation. Manifestations of intracranial hypertension include bulging fontanelles, headaches, and bilateral papilledema.

Administration of topical corticosteroids to children should be limited to the least amount compatible with an effective therapeutic regimen. Chronic corticosteroid therapy may interfere with the growth and development of children.

Geriatric Use

Of approximately 3000 patients included in clinical studies of 0.1% HALOG CREAM, 14% were 60 years or older, while 4% were 70 years or older. No overall differences in safety were observed between these patients and younger patients. Efficacy data have not been evaluated for differences between elderly and younger patients. Other reported clinical experience has not identified differences in responses between the elderly and younger patients, but greater sensitivity of some older individuals cannot be ruled out.

ADVERSE REACTIONS

The following local adverse reactions are reported infrequently with topical corticosteroids, but may occur more frequently with the use of occlusive dressings (reactions are listed in an approximate decreasing order of occurrence): burning, itching, irritation, dryness, folliculitis, hypertrichosis, acneiform eruptions, hypopigmentation, perioral dermatitis, allergic contact dermatitis, maceration of the skin, secondary infection, skin atrophy, striae, and miliaria.

OVERDOSAGE

Topically applied corticosteroids can be absorbed in sufficient amounts to produce systemic effects (see PRECAUTIONS: General).

DOSAGE AND ADMINISTRATION SECTION

Apply the 0.1% HALOG (Halcinonide Cream, USP) to the affected area two to three times daily. Rub in gently.

Occlusive Dressing Technique

Occlusive dressings may be used for the management of psoriasis or other recalcitrant conditions. Gently rub a small amount of cream into the lesion until it disappears. Reapply the preparation leaving a thin coating on the lesion, cover with a pliable nonporous film, and seal the edges. If needed, additional moisture may be provided by covering the lesion with a dampened clean cotton cloth before the non-porous film is applied or by briefly wetting the affected area with water immediately prior to applying the medication. The frequency of changing dressings is best determined on an individual basis. It may be convenient to apply HALOG under an occlusive dressing in the evening and to remove the dressing in the morning (i.e., 12-hour occlusion). When utilizing the 12-hour occlusion regimen, additional cream should be applied, without occlusion, during the day. Reapplication is essential at each dressing change.

If an infection develops, the use of occlusive dressings should be discontinued and appropriate antimicrobial therapy instituted.

HOW SUPPLIED

HALOG® (Halcinonide Cream, USP) 0.1% is smooth, soft homogeneous white to off-white cream, essentially free of foreign matter and is supplied as:

NDC 64950-126-06 Tube containing 60 g

Storage

Store at room temperature; avoid excessive heat (104° F).

To report SUSPECTED ADVERSE REACTIONS, contact the FDA at 1-800-FDA-1088 or www.fda.gov/medwatch.

Distributed by:

Genus Lifesciences Inc.
Allentown, PA 18102

5261106

Rev. 05/2025